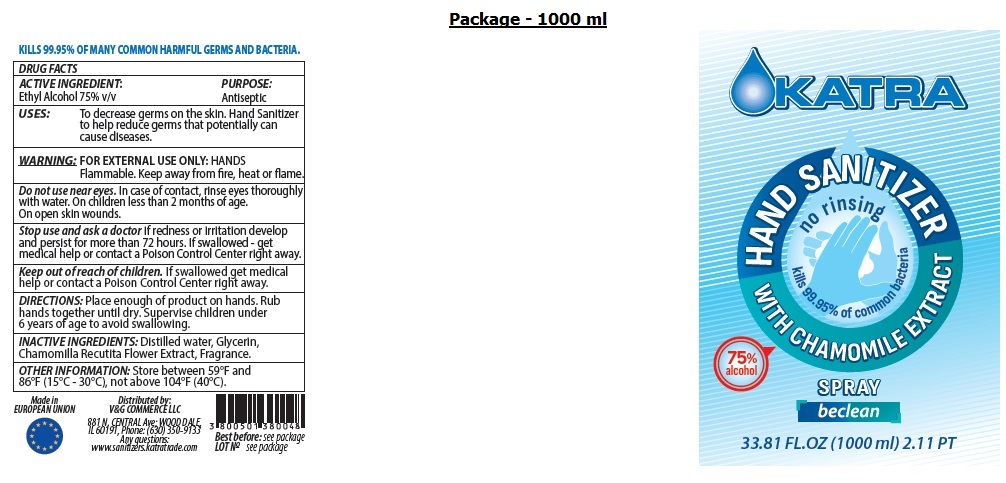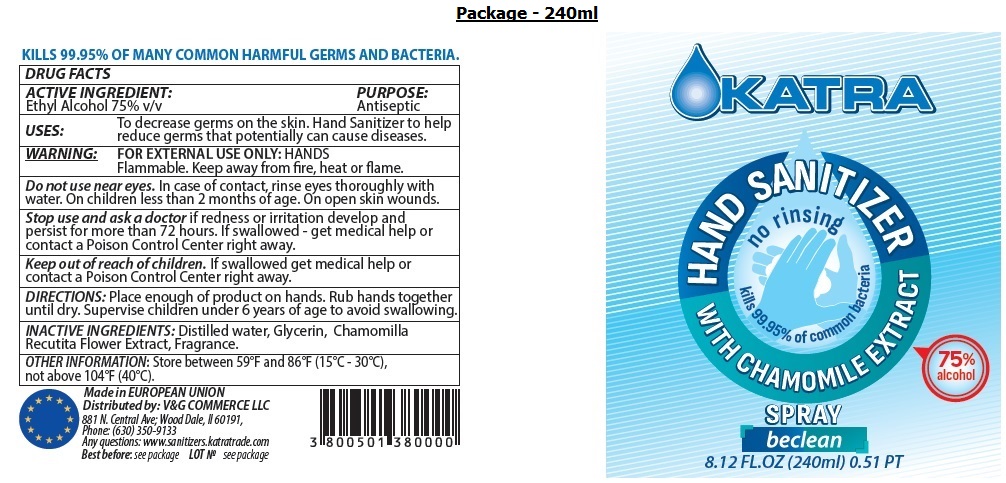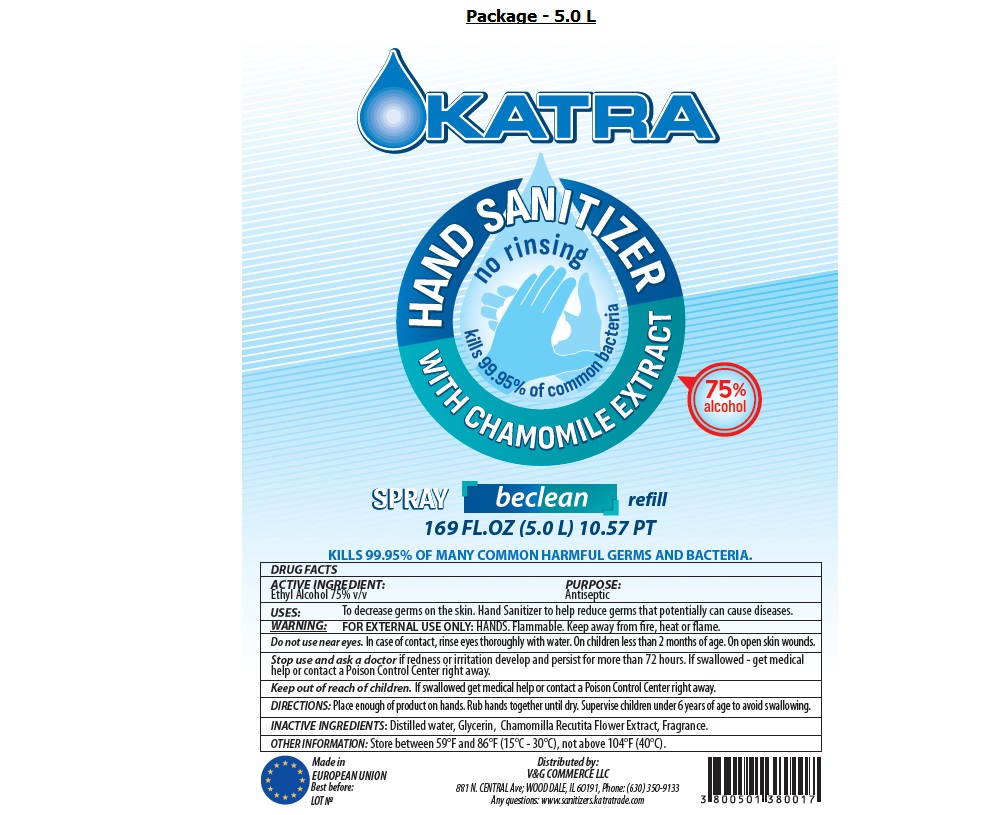 DRUG LABEL: KATRA HAND SANITIZER
NDC: 81103-002 | Form: SPRAY
Manufacturer: THS COSMETIC EOOD
Category: otc | Type: HUMAN OTC DRUG LABEL
Date: 20201123

ACTIVE INGREDIENTS: ALCOHOL 75 mL/100 mL
INACTIVE INGREDIENTS: WATER; GLYCERIN; CHAMOMILE

KATRA HAND SANITIZER SPRAY

ACTIVE INGREDIENT:

Ethyl Alcohol 75% v/v

PURPOSE:

Antiseptic

USES:

To decrease germs on the skin. Hand Sanitizer to help reduce germs that potentially can cause diseases.

WARNING:

FOR EXTERNAL USE ONLY: HANDS
Flammable. Keep away from fire, heat or flame.

Do not use near eyes. In case of contact, rinse eyes thoroughly with water. On children less than 2 months of age. On open skin wounds.
Stop use and ask a doctor if redness or irritation develop and persist for more than 72 hours. If swallowed - get medical help or contact a Poison Control Center right away.

Keep out of reach of children. If swallowed get medical help or contact a Poison Control Center right away.

DIRECTIONS:

Place enough of product on hands. Rub hands together until dry. Supervise children under 6 years of age to avoid swallowing.

OTHER INFORMATION:

Store between 59°F and 86°F (15°C - 30°C), not above 104°F (40°C).

INACTIVE INGREDIENTS:

Distilled water, Glycerin, Chamomilla Recutita Flower Extract, Fragrance.

WITH CHAMOMILE EXTRACT

no rinsing

kills 99.95% of common bacteria

75% alcohol

beclean

KILLS 99.95% OF MANY COMMON HARMFUL GERMS AND BACTERIA.

Made in EUROPEAN UNION

Distributed by: V&G COMMERCE LLC

881 N. Central Ave; Wood Dale, Il 60191,

Phone: (630) 350-9133

Any questions: www.sanitizers.katratrade.com